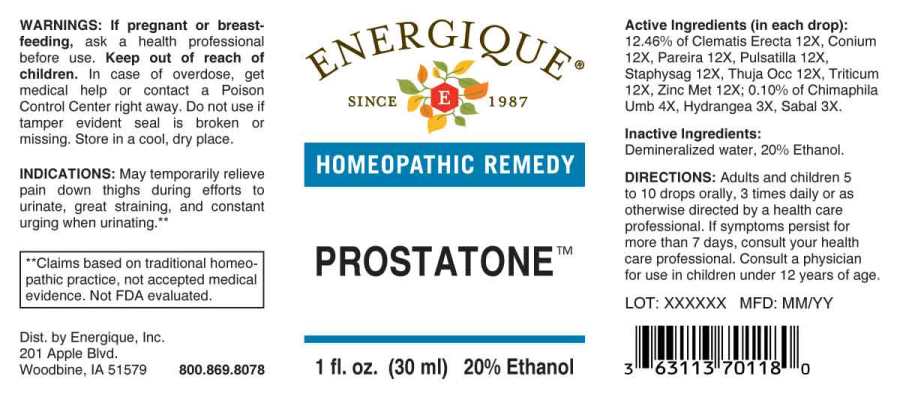 DRUG LABEL: Prostatone
NDC: 44911-0494 | Form: LIQUID
Manufacturer: Energique, Inc.
Category: homeopathic | Type: HUMAN OTC DRUG LABEL
Date: 20241029

ACTIVE INGREDIENTS: HYDRANGEA ARBORESCENS ROOT 3 [hp_X]/1 mL; SAW PALMETTO 3 [hp_X]/1 mL; CHIMAPHILA UMBELLATA WHOLE 4 [hp_X]/1 mL; CLEMATIS RECTA FLOWERING TOP 12 [hp_X]/1 mL; CONIUM MACULATUM FLOWERING TOP 12 [hp_X]/1 mL; CHONDRODENDRON TOMENTOSUM ROOT 12 [hp_X]/1 mL; PULSATILLA PRATENSIS 12 [hp_X]/1 mL; THUJA OCCIDENTALIS LEAFY TWIG 12 [hp_X]/1 mL; ELYMUS REPENS ROOT 12 [hp_X]/1 mL; DELPHINIUM STAPHISAGRIA SEED 12 [hp_X]/1 mL; ZINC 12 [hp_X]/1 mL
INACTIVE INGREDIENTS: WATER; ALCOHOL

DRUG FACTS:

ACTIVE INGREDIENTS:

(in each drop): 12.46% of Clematis Erecta 12X, Conium Maculatum 12X, Pareira Brava 12X, Pulsatilla (Pratensis) 12X, Staphysagria 12X, Thuja Occidentalis 12X, Triticum Repens 12X, Zincum Metallicum 12X; 0.10% of Chimaphila Umbellata 4X, Hydrangea Arborescens 3X, Sabal Serrulata 3X.

INDICATIONS:

May temporarily relieve pain down thighs during efforts to urinate, great straining and constant urging when urinating.**

**Claims based on traditional homeopathic practice, not accepted medical evidence. Not FDA evaluated.

WARNINGS:

If pregnant or breastfeeding, ask a health professional before use.

Keep out of reach of children. In case of overdose, get medical help or contact a Poison Control Center right away.

Do not use if tamper evident seal is broken or missing.

Store in a cool, dry place.

Keep out of reach of children. In case of overdose, get medical help or contact a Poison Control Center right away.

DIRECTIONS:

Adults and children 5 to 10 drops orally, 3 times daily or as otherwise directed by a health care professional. If symptoms persist for more than 7 days, consult your health care professional. Consult a physician for use in children under 12 years of age.

INDICATIONS:

May temporarily relieve pain down thighs during efforts to urinate, great straining and constant urging when urinating.**

**Claims based on traditional homeopathic practice, not accepted medical evidence. Not FDA evaluated.

INACTIVE INGREDIENTS:

Demineralized water, 20% Ethanol.

QUESTIONS:

Dist. by Energique, Inc.
201 Apple Blvd.
Woodbine, IA 51579 800.868.8078

PACKAGE LABEL DISPLAY:

ENERGIQUE

SINCE 1987

HOMEOPATHIC REMEDY

PROSTATONE

1 fl. oz. (30 ml)